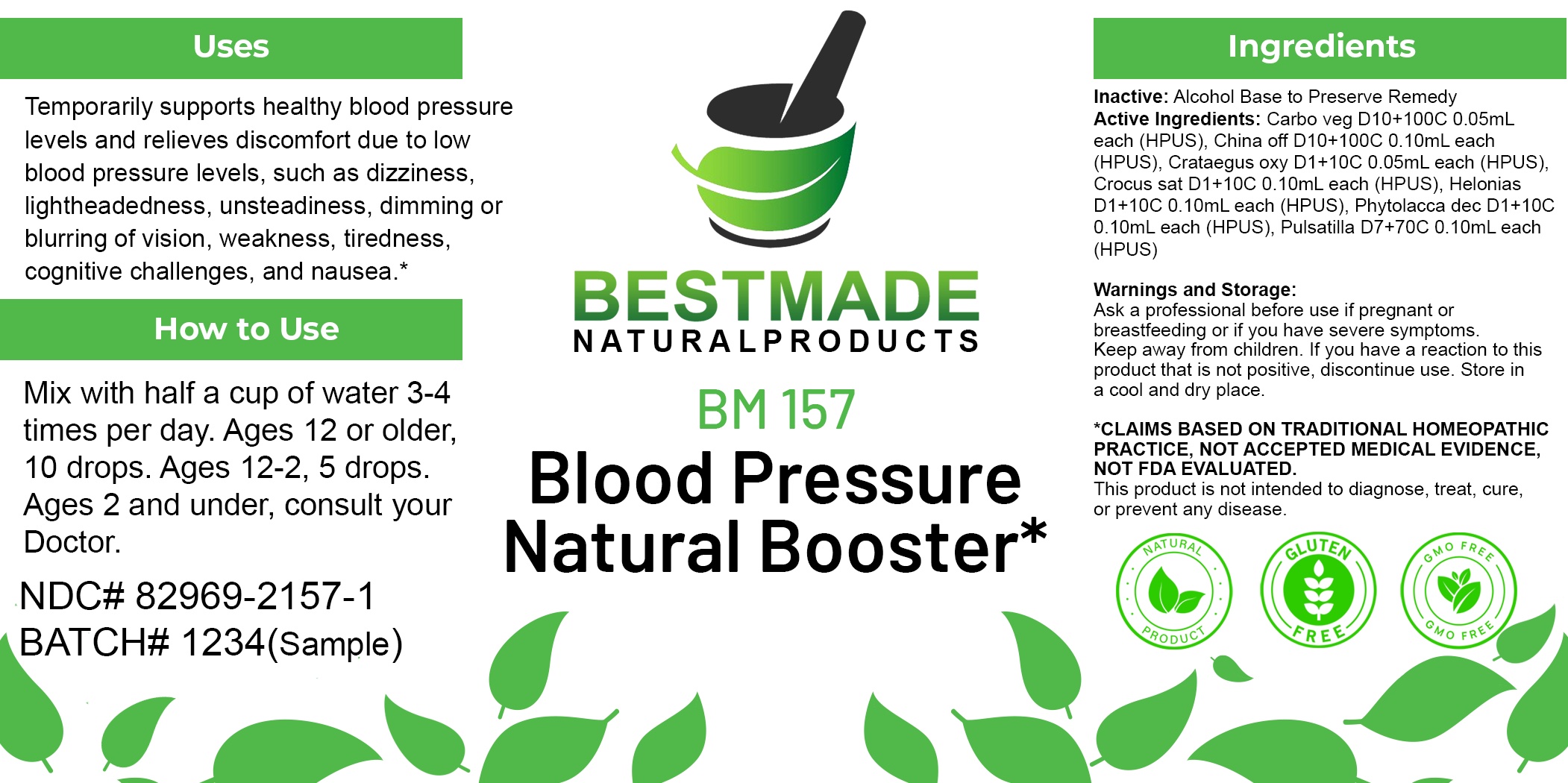 DRUG LABEL: Bestmade Natural Products BM157
NDC: 82969-2157 | Form: LIQUID
Manufacturer: Bestmade Natural Products
Category: homeopathic | Type: HUMAN OTC DRUG LABEL
Date: 20250218

ACTIVE INGREDIENTS: SAFFRON 30 [hp_C]/30 [hp_C]; CHAMAELIRIUM LUTEUM ROOT 30 [hp_C]/30 [hp_C]; PULSATILLA PRATENSIS 30 [hp_C]/30 [hp_C]; PHYTOLACCA AMERICANA ROOT 30 [hp_C]/30 [hp_C]; CINCHONA OFFICINALIS BARK 30 [hp_C]/30 [hp_C]; ACTIVATED CHARCOAL 30 [hp_C]/30 [hp_C]; CRATAEGUS OXYACANTHA LEAF 30 [hp_C]/30 [hp_C]
INACTIVE INGREDIENTS: ALCOHOL 30 [hp_C]/30 [hp_C]

BM157

ACTIVE INGREDIENTS:

Carbo veg D10+100C 0.05mL each (HPUS), China off D10+100C 0.10mL each (HPUS), Crataegus oxy D1+10C 0.05mL each (HPUS), Crocus sat D1+10C 0.10mL each (HPUS), Helonias D1+10C 0.10mL each (HPUS), Phytolacca dec D1+10C 0.10mL each (HPUS), Pulsatilla D7+70C 0.10mL each (HPUS)

Inactive:

Alcohol Base to Preserve Product

DOSAGE AND ADMINISTRATION

How to Use

Mix with half a cup of water 3-4 times per day. Ages 12 or older, 10 drops. Ages 12-2, 5 drops. Ages 2 and under, consult your Doctor.

Uses
Temporarily supports healthy blood pressure levels and relieves discomfort due to low blood pressure levels, such as dizziness,
lightheadedness, unsteadiness, dimming or blurring of vision, weakness, tiredness, cognitive challenges, and nausea.*

Uses
Temporarily supports healthy blood pressure levels and relieves discomfort due to low blood pressure levels, such as dizziness,
lightheadedness, unsteadiness, dimming or blurring of vision, weakness, tiredness, cognitive challenges, and nausea.*

KEEP OUT OF REACH OF CHILDREN

Warnings and Storage:

Ask a professional before use if pregnant or breastfeeding or if you have severe symptoms.

Keep away from children. If you have a reaction to this product that is not positive, discontinue use. Store in a cool and dry place

*CLAIMS BASED ON TRADITIONAL HOMEOPATHIC PRACTICE, NOT ACCEPTED MEDICAL EVIDENCE NOT FDA EVALUATED.
This product is not intended to diagnose, treat, cure, or prevent any disease.

Warnings and Storage:

Ask a professional before use if pregnant or breastfeeding or if you have severe symptoms.

Keep away from children. If you have a reaction to this product that is not positive, discontinue use. Store in a cool and dry place

*CLAIMS BASED ON TRADITIONAL HOMEOPATHIC PRACTICE, NOT ACCEPTED MEDICAL EVIDENCE NOT FDA EVALUATED.
This product is not intended to diagnose, treat, cure, or prevent any disease.

Entire package label.